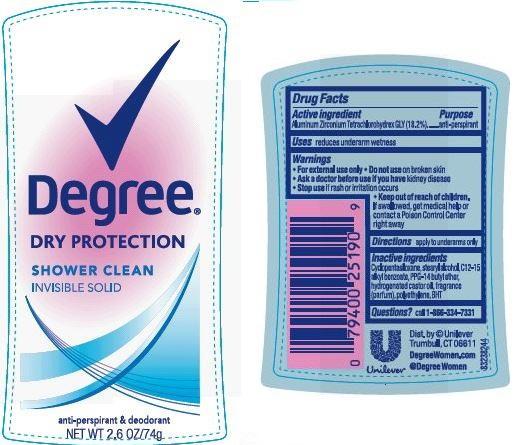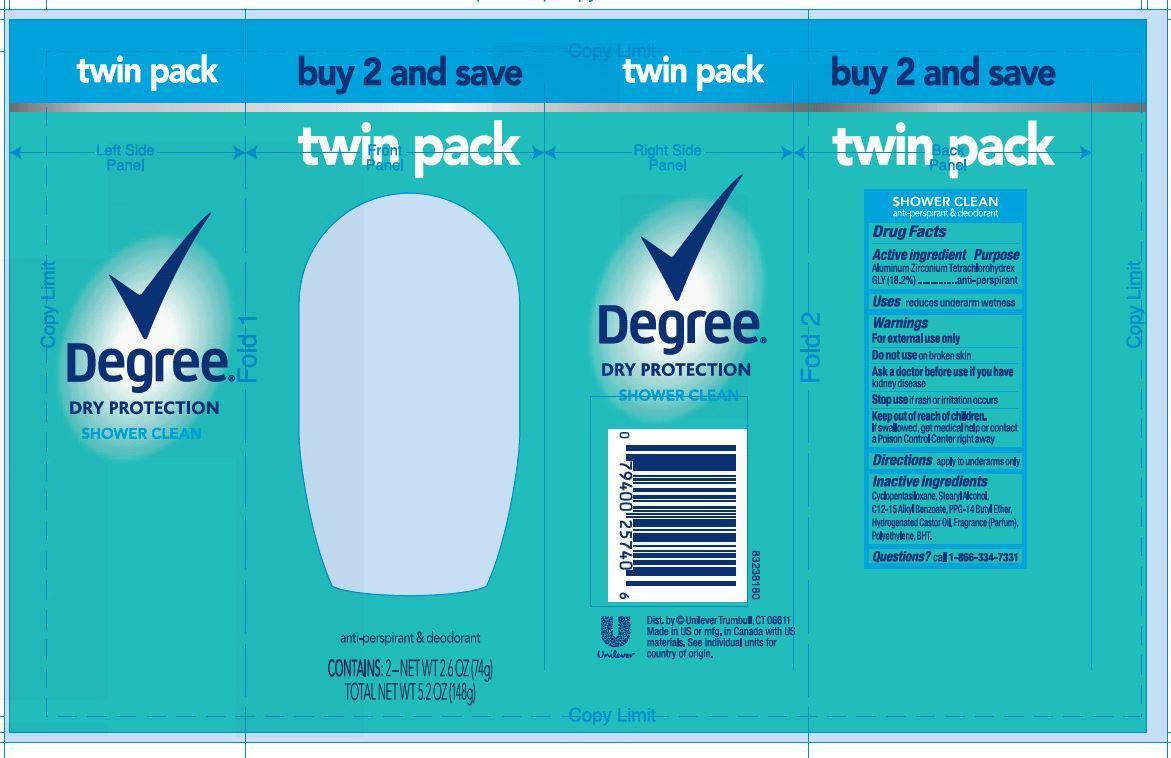 DRUG LABEL: Degree
NDC: 64942-1995 | Form: STICK
Manufacturer: Conopco Inc. d/b/a Unilever
Category: otc | Type: HUMAN OTC DRUG LABEL
Date: 20241108

ACTIVE INGREDIENTS: ALUMINUM ZIRCONIUM TETRACHLOROHYDREX GLY 18.2 g/100 g
INACTIVE INGREDIENTS: CYCLOMETHICONE 5; STEARYL ALCOHOL; ALKYL (C12-15) BENZOATE; PPG-14 BUTYL ETHER; HYDROGENATED CASTOR OIL; BUTYLATED HYDROXYTOLUENE; HIGH DENSITY POLYETHYLENE

Degree Shower Clean Antiperspirant Deodorant

Active Ingredient

Aluminum Zirconium Tetrachlorohydrex GLY (18.2%)

Purpose
anti-perspirant

Warnings
For external use only

Do not use on broken skin

Ask a doctor before use if you have kidney disease

Stop use if rash or irritation occurs

Keep out of reach of children. If swallowed, get medical help or contact a Poison Control Center right away.

Uses
reduces underarm wetness

Inactive ingredients
Cyclopentasiloxane, Stearyl Alcohol, C12-15 Alkyl Benzoate, PPG-14 Butyl Ether, Hydrogenated Castor Oil, Fragrance (Parfum), Polyethylene, BHT.

Directions

apply to underarms only

Questions? Call toll-free 1-866-334-7331